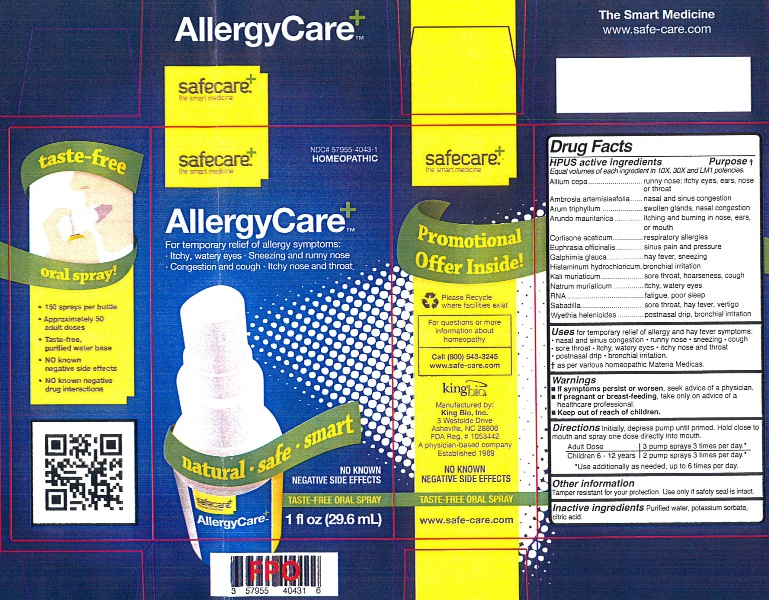 DRUG LABEL: AllergyCare
NDC: 57955-4043 | Form: LIQUID
Manufacturer: King Bio Inc.
Category: homeopathic | Type: HUMAN OTC DRUG LABEL
Date: 20120613

ACTIVE INGREDIENTS: ONION 10 [hp_X]/29.6 mL; AMBROSIA ARTEMISIIFOLIA 10 [hp_X]/29.6 mL; ARISAEMA TRIPHYLLUM ROOT 10 [hp_X]/29.6 mL; ARUNDO PLINIANA ROOT 10 [hp_X]/29.6 mL; CORTISONE ACETATE 10 [hp_X]/29.6 mL; EUPHRASIA STRICTA 10 [hp_X]/29.6 mL; GALPHIMIA GLAUCA FLOWERING TOP 10 [hp_X]/29.6 mL; HISTAMINE DIHYDROCHLORIDE 10 [hp_X]/29.6 mL; POTASSIUM CHLORIDE 10 [hp_X]/29.6 mL; SODIUM CHLORIDE 10 [hp_X]/29.6 mL; SACCHAROMYCES CEREVISIAE RNA 10 [hp_X]/29.6 mL; SCHOENOCAULON OFFICINALE SEED 10 [hp_X]/29.6 mL; WYETHIA HELENIOIDES ROOT 10 [hp_X]/29.6 mL
INACTIVE INGREDIENTS: WATER; POTASSIUM SORBATE; CITRIC ACID MONOHYDRATE

AllergyCare

Active Ingredients

Drug Facts

HPUS active ingredients

Equal volumes of each ingredient in 10X, 30X and LM1 potencies.

Allium cepa, Ambrosia artemisiaefolia, Arum triphyllum, Arundo mauritanica, Cortisone aceticum, Euphrasia officinalis, Galphimia glauca, Histaminum hydrochloricum, Kali muriaticum, Natrum muriaticum, RNA, Sabadilla and Wyethia helenioides.

Reference image allergycare.jpg

Inactive Ingredients

Purified water, potassium sorbate and citric acid.

Reference image allergycare.jpg

Purpose

Drug Facts

HPUS active ingredients Purpose

Equal volumes of each ingredient in 10X, 30X and LM1 potencies.

Allium cepa...........................................................runny nose; itchy eyes, ears, nose or throat

Ambrosia artemisiaefolia........................................nasal and sinus congestion

Arum triphyllum......................................................swollen glands, nasal congestion

Arundo mauritanica...............................................itching and burning in nose, ears, or mouth

Cortisone aceticum...............................................respiratory allergies

Euphrasia officinalis..............................................sinus pain and pressure

Galphimia glauca...................................................hay fever, sneezing

Histaminum hydrochloricum...................................bronchial irritation

Kali muriaticum.....................................................sore throat, hoarseness, cough

Natrum muriaticum...............................................itchy, watery eyes

RNA....................................................................fatigue, poor sleep

Sabadilla..............................................................sore throat, hay fever, vertigo

Wyethia helenioides............................................postnasal drip, bronchial irritation

Reference image allergycare.jpg

Dosage and Administration

Directions Initially, depress pump until primed. Hold close to mouth and spray one dose directly into mouth.

Adult Dose 3 pump sprays 3 times per day.

Children 6 - 12 years 2 pump sprays 3 times per day.

Use additionally as needed, up to 6 times per day.

Reference image allergycare.jpg

Warnings

- If symptoms persist or worsen, seek advice of a physician.

- If pregnant or breast-feeding, take only on advice of a healthcare professional.

- Keep out of reach of children.

Other information: Tamper resistant for your protection. Use only if safety seal is intact.
Reference image allergycare.jpg

Keep out of reach of children.

Reference image allergycare.jpg

Indications and Usage

Uses for temporary relief of allergy and hay fever symptoms:

- nasal and sinus congestion
- runny nose
- sneezing
- cough
- sore throat
- itchy, watery eyes
- itchy nose and throat
- postnasal drip
- bronchial irritation

as per various homeopathic Materia Medicas.
Reference image allergycare.jpg

PACKAGE LABEL

King Bio Inc.

3 Westside Drive

Asheville, NC 28806

For questions or more information about homeopathy call 800.543-3245 or www.safe-care.com